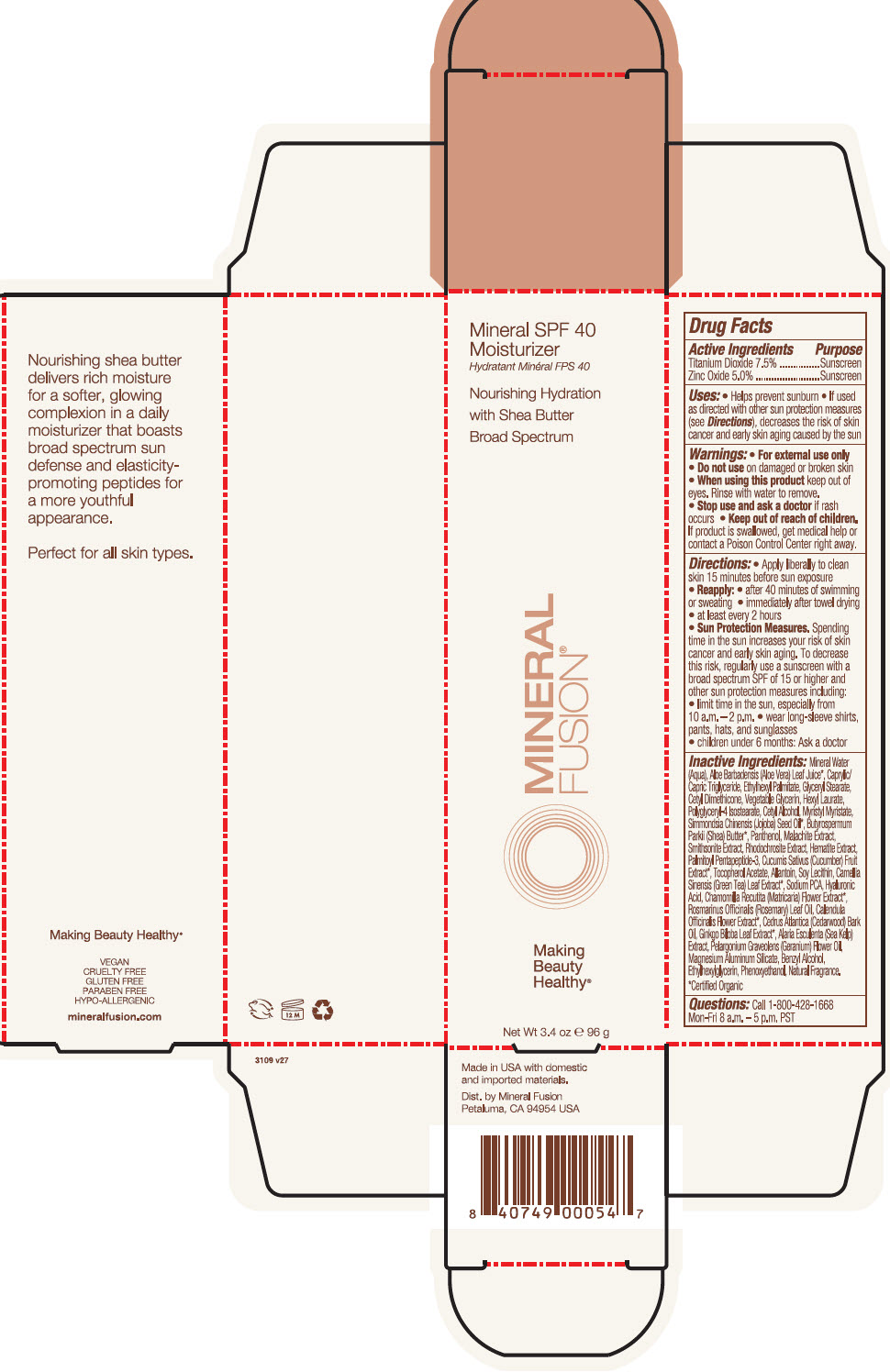 DRUG LABEL: Mineral SPF 40 Moisturizer
NDC: 55789-3109 | Form: LOTION
Manufacturer: Mineral Fusion brands
Category: otc | Type: HUMAN OTC DRUG LABEL
Date: 20190917

ACTIVE INGREDIENTS: ZINC OXIDE 5 g/100 mL; TITANIUM DIOXIDE 7.5 g/100 mL
INACTIVE INGREDIENTS: ETHYLHEXYL PALMITATE; GLYCERYL MONOSTEARATE; CETYL DIMETHICONE 25; GLYCERIN; HEXYL LAURATE; ALOE VERA LEAF; POLYGLYCERYL-4 ISOSTEARATE; MEDIUM-CHAIN TRIGLYCERIDES; CETYL ALCOHOL; SHEA BUTTER; PANTHENOL; MAGNESIUM ASPARTATE; ZINC GLUCONATE; JOJOBA OIL; TOCOPHEROL; COPPER GLUCONATE; HYALURONATE SODIUM; PALMITOYL PENTAPEPTIDE-4; ETHYLHEXYLGLYCERIN; ALLANTOIN; SODIUM PYRROLIDONE CARBOXYLATE; LECITHIN, SOYBEAN; MAGNESIUM ALUMINUM SILICATE; GREEN TEA LEAF; PHENOXYETHANOL

Mineral SPF 40 Moisturizer

Drug Facts

ACTIVE INGREDIENT

Active Ingredients | Purpose
Titanium Dioxide 7.5% | Sunscreen
Zinc Oxide 5.0% | Sunscreen

Uses

- Helps prevent sunburn
- If used as directed with other sun protection measures (see Directions), decreases the risk of skin cancer and early skin aging caused by the sun

Warnings

- For external use only

- Do not use on damaged or broken skin

- When using this product keep out of eyes. Rinse with water to remove.

- Stop use and ask a doctor if rash occurs

- Keep out of reach of children. If product is swallowed, get medical help or contact a Poison Control Center right away.

Directions

- Apply liberally to clean skin 15 minutes before sun exposure
- Reapply:
  - after 40 minutes of swimming or sweating
  - immediately after towel drying
  - at least every 2 hours
- Sun Protection Measures. Spending time in the sun increases your risk of skin cancer and early skin aging. To decrease this risk, regularly use a sunscreen with a broad spectrum SPF of 15 or higher and other sun protection measures including:
  - limit time in the sun, especially from 10 a.m. – 2 p.m.
  - wear long-sleeve shirts, pants, hats, and sunglasses
- children under 6 months: Ask a doctor

Inactive Ingredients

Mineral Water (Aqua), Aloe Barbadensis (Aloe Vera) Leaf Juice [Certified Organic] Caprylic/Capric Triglyceride, Ethylhexyl Palmitate, Glyceryl Stearate, Cetyl Dimethicone, Vegetable Glycerin, Hexyl Laurate, Polyglyceryl-4 Isostearate, Cetyl Alcohol, Myristyl Myristate, Simmondsia Chinensis (Jojoba) Seed Oil Butyrospermum Parkii (Shea) Butter, Panthenol, Malachite Extract, Smithsonite Extract, Rhodochrosite Extract, Hematite Extract, Palmitoyl Pentapeptide-3, Cucumis Sativus (Cucumber) Fruit Extract, Tocopherol Acetate, Allantoin, Soy Lecithin, Camellia Sinensis (Green Tea) Leaf Extract, Sodium PCA, Hyaluronic Acid, Chamomilla Recutita (Matricaria) Flower Extract, Rosmarinus Officinalis (Rosemary) Leaf Oil, Calendula Officinalis Flower Extract, Cedrus Atlantica (Cedarwood) Bark Oil, Ginkgo Biloba Leaf Extract, Alaria Esculenta (Sea Kelp) Extract, Pelargonium Graveolens (Geranium) Flower Oil, Magnesium Aluminum Silicate, Benzyl Alcohol, Ethylhexylglycerin, Phenoxyethanol, Natural Fragrance.

Questions

Call 1-800-428-1668
Mon-Fri 8 a.m. – 5 p.m. PST

Dist. by Mineral Fusion
Petaluma, CA 94954 USA

PRINCIPAL DISPLAY PANEL - 96 g Tube Carton

Mineral SPF 40
Moisturizer

Nourishing Hydration
with Shea Butter
Broad Spectrum

MINERAL
FUSION®

Making
Beauty
Healthy®

Net Wt 3.4 oz e 96 g